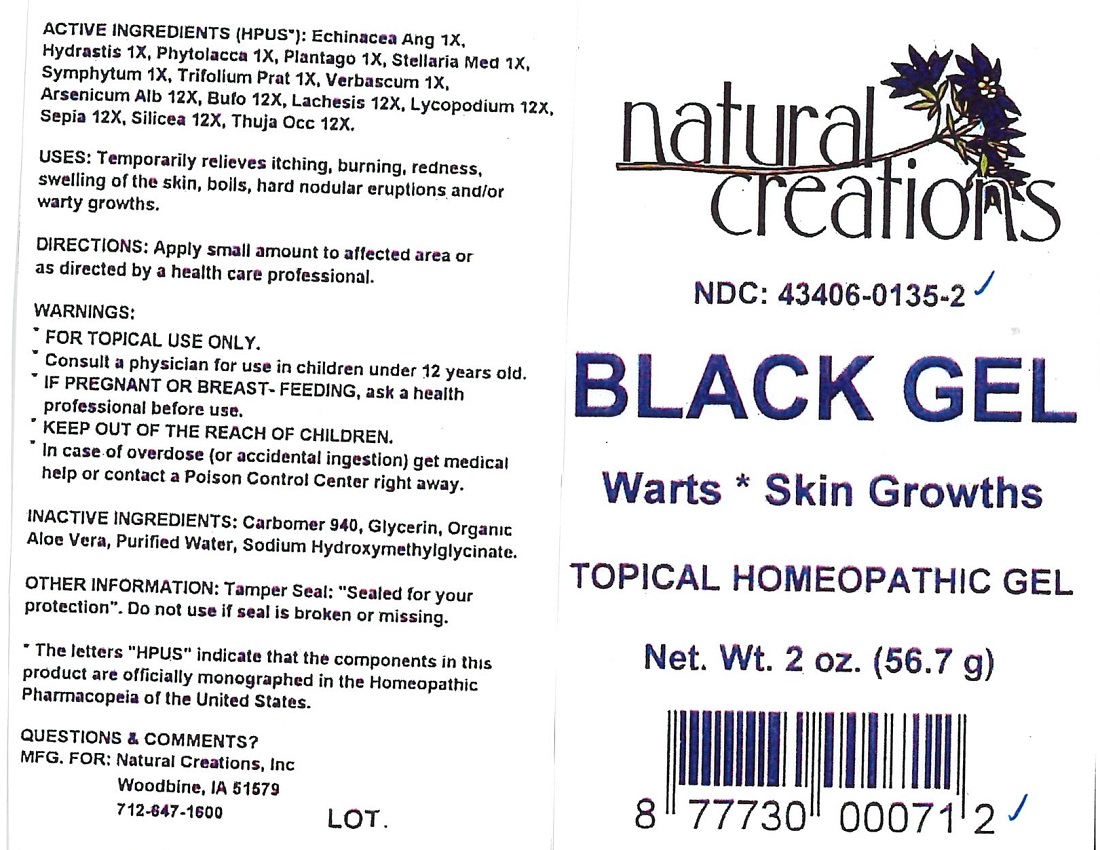 DRUG LABEL: BLACK
NDC: 43406-0135 | Form: GEL
Manufacturer: Natural Creations, Inc
Category: homeopathic | Type: HUMAN OTC DRUG LABEL
Date: 20181221

ACTIVE INGREDIENTS: ECHINACEA ANGUSTIFOLIA WHOLE 1 [hp_X]/1 g; GOLDENSEAL 1 [hp_X]/1 g; PHYTOLACCA AMERICANA ROOT 1 [hp_X]/1 g; PLANTAGO MAJOR WHOLE 1 [hp_X]/1 g; STELLARIA MEDIA 1 [hp_X]/1 g; COMFREY LEAF 1 [hp_X]/1 g; TRIFOLIUM PRATENSE FLOWER 1 [hp_X]/1 g; VERBASCUM THAPSUS WHOLE 1 [hp_X]/1 g; ARSENIC TRIOXIDE 12 [hp_X]/1 g; BUFO BUFO CUTANEOUS GLAND 12 [hp_X]/1 g; LACHESIS MUTA VENOM 12 [hp_X]/1 g; LYCOPODIUM CLAVATUM SPORE 12 [hp_X]/1 g; SEPIA OFFICINALIS JUICE 12 [hp_X]/1 g; SILICON DIOXIDE 12 [hp_X]/1 g; THUJA OCCIDENTALIS LEAFY TWIG 12 [hp_X]/1 g
INACTIVE INGREDIENTS: CARBOMER 940; GLYCERIN; ALOE VERA LEAF; WATER; SODIUM HYDROXYMETHYLGLYCINATE

BLACK

ACTIVE INGREDIENT

ACTIVE INGREDIENTS: (HPUS*): Echinacea Ang 1X, Hydrastis 1X, Phytolacca 1X, Plantago 1X, Stellaria Med 1X, Symphytum 1X, Trifolium Prat 1X, Verbascum 1X, Arsenicum Alb 12X, Bufo 12X, Lachesis 12X, Lycopodium 12X, Sepia 12X, Silicea 12X, Thuja Occ 12X.

INDICATIONS AND USAGE

USES: Temporarily relieves itching, burning, and redness, swelling of the skin, boils, hard nodular eruptions and/or warty growths.

PURPOSE

USES: Temporarily relieves itching, burning, and redness, swelling of the skin, boils, hard nodular eruptions and/or warty growths.

DOSAGE AND ADMINISTRATION

DIRECTIONS: Apply a small amount to affected area or as directed by a health care professional.

KEEP OUT OF REACH OF CHILDREN

KEEP OUT OF THE REACH OF CHILDREN. In case of overdose (or accidental ingestion) get medical help or contact a Poison Control Center right away.

WARNINGS:

- FOR TOPICAL USE ONLY.
- Consult a physician for use in children under 12 years of age.
- IF PREGNANT OR BREAST-FEEDING, ask a health care professional before use.
- KEEP OUT OF THE REACH OF CHILDREN. In case of overdose (or accidental ingestion) get medical help or contact a Poison Control Center right away.
- Do not use if TAMPER EVIDENT seal is broken or missing.

INACTIVE INGREDIENT

INACTIVE INGREDIENTS: Carbomer 940, Glycerin, Organic Aloe Vera, Purified Water, Sodium Hydroxmethylglycinate.

QUESTIONS & COMMENTS?

Natural Creations, Inc. / Woodbine, IA 51579 / 712-647-1600

REFERENCES

**The letters "HPUS" indicate the components in this product are officially monographed in the Homeopathic Pharmacopeia of the United States.

PACKAGE LABEL

NDC: 43406-0135-2

BLACK GEL

Warts*Skin Growths

TOPICAL HOMEOPATHIC GEL

Net. Wt. 2oz. (56.7g)